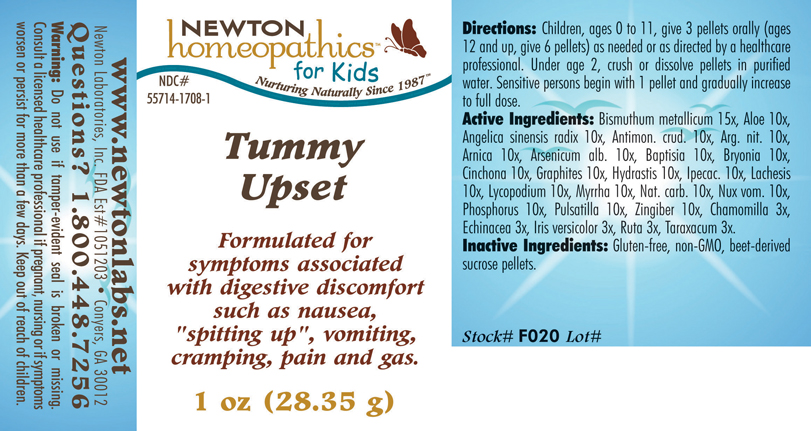 DRUG LABEL: Tummy Upset 
NDC: 55714-1708 | Form: PELLET
Manufacturer: Newton Laboratories, Inc.
Category: homeopathic | Type: HUMAN OTC DRUG LABEL
Date: 20110301

ACTIVE INGREDIENTS: Bismuth 15 [hp_X]/1 g; Aloe 10 [hp_X]/1 g; Angelica Sinensis Root 10 [hp_X]/1 g; Antimony Trisulfide 10 [hp_X]/1 g; Silver Nitrate 10 [hp_X]/1 g; Arnica Montana 10 [hp_X]/1 g; Arsenic Trioxide 10 [hp_X]/1 g; Baptisia Tinctoria 10 [hp_X]/1 g; Bryonia Alba Root 10 [hp_X]/1 g; Cinchona Officinalis Bark 10 [hp_X]/1 g; Graphite 10 [hp_X]/1 g; Goldenseal 10 [hp_X]/1 g; Ipecac 10 [hp_X]/1 g; Lachesis Muta Venom 10 [hp_X]/1 g; Lycopodium Clavatum Spore 10 [hp_X]/1 g; Myrrh 10 [hp_X]/1 g; Sodium Carbonate 10 [hp_X]/1 g; Strychnos Nux-vomica Seed 10 [hp_X]/1 g; Phosphorus 10 [hp_X]/1 g; Pulsatilla Vulgaris 10 [hp_X]/1 g; Ginger 10 [hp_X]/1 g; Matricaria Recutita 3 [hp_X]/1 g; Echinacea, Unspecified 3 [hp_X]/1 g; Iris Versicolor Root 3 [hp_X]/1 g; Ruta Graveolens Flowering Top 3 [hp_X]/1 g; Taraxacum Officinale 3 [hp_X]/1 g
INACTIVE INGREDIENTS: Sucrose

Tummy Upset

INDICATIONS & USAGE SECTION

Tummy Upset Formulated for symptoms associated with digestive discomfort such as nausea, "spitting up", vomiting, cramping, pain and gas.

DOSAGE & ADMINISTRATION SECTION

Directions: Children, ages 0 to 11, give 3 pellets orally (ages 12 and up, give 6 pellets) as needed or as directed by a healthcare professional. Under age 2, crush or dissolve pellets in purified water. Sensitive persons begin with 1 pellet and gradually increase to full dose.

OTC - ACTIVE INGREDIENT SECTION

Bismuthum metallicum 15x, Aloe 10x, Angelica sinensis radix 10x, Antimon. crud. 10x, Arg. nit. 10x, Arnica 10x, Arsenicum alb. 10x, Baptisia 10x, Bryonia 10x, Cinchona 10x, Graphites 10x, Hydrastis 10x, Ipecac. 10x, Lachesis 10x, Lycopodium 10x, Myrrha 10x, Nat. carb. 10x, Nux vom. 10x, Phosphorus 10x, Pulsatilla 10x, Zingiber 10x, Chamomilla 3x, Echinacea 3x, Iris versicolor 3x, Ruta 3x, Taraxacum 3x.

OTC - PURPOSE SECTION

Formulated for symptoms associated with digestive discomfort such as nausea,"spitting up", vomiting, cramping, pain and gas.

INACTIVE INGREDIENT SECTION

Inactive Ingredients: Gluten-free, non-GMO, beet-derived sucrose pellets.

QUESTIONS SECTION

www.newtonlabs.net Newton Laboratories, Inc. FDA Est # 1051203 - Conyers, GA 30012
Questions? 1.800.448.7256

WARNINGS SECTION

Warning: Do not use if tamper - evident seal is broken or missing. Consult a licensed healthcare professional if pregnant, nursing or if symptoms worsen or persist for more than a few days. Keep out of reach of children.

OTC - PREGNANCY OR BREAST FEEDING SECTION

Consult a licensed healthcare professional if pregnant, nursing or if symptoms worsen or persist for more than a few days.

OTC - KEEP OUT OF REACH OF CHILDREN SECTION

Keep out of reach of children.